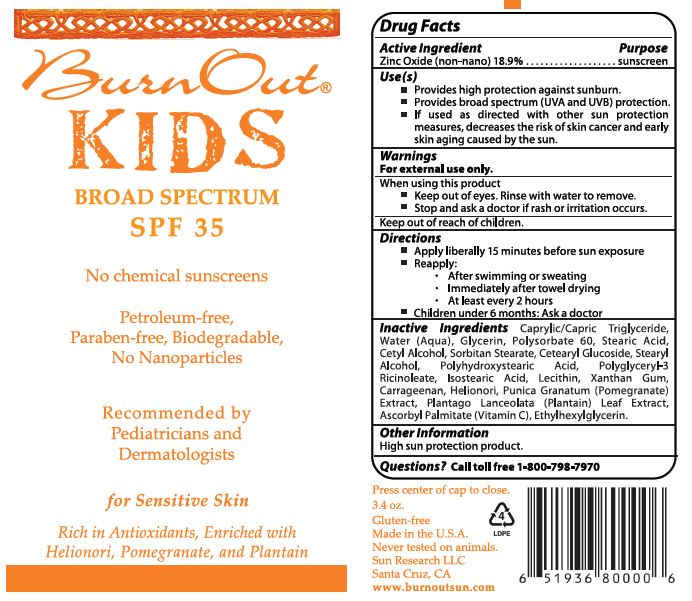 DRUG LABEL: Kids Broad Spectrum SPF 35
NDC: 62742-4114 | Form: CREAM
Manufacturer: Allure Labs, LLC
Category: otc | Type: HUMAN OTC DRUG LABEL
Date: 20241205

ACTIVE INGREDIENTS: ZINC OXIDE 189 mg/1 g
INACTIVE INGREDIENTS: PLANTAGO LANCEOLATA LEAF; ASCORBYL PALMITATE; SORBITAN MONOSTEARATE; CETEARYL GLUCOSIDE; CETYL ALCOHOL; ETHYLHEXYLGLYCERIN; GLYCERIN; PORPHYRA UMBILICALIS; CARRAGEENAN; WATER; STEARYL ALCOHOL; POLYHYDROXYSTEARIC ACID STEARATE; ISOSTEARIC ACID; PUNICA GRANATUM ROOT BARK; MEDIUM-CHAIN TRIGLYCERIDES; POLYSORBATE 60; STEARIC ACID; POLYGLYCERYL-3 RICINOLEATE; LECITHIN, SOYBEAN; XANTHAN GUM

Drug Facts

Active Ingredients:

Zinc Oxide 18.9%

Purpose

Sunscreen

Uses:

- Provide high protection against sunburn.
- Provide broad spectrum (UVA and UVB) protection.
- If used as directed with other sun protection measures, decreases the risk of skin cancer and early skin aging caused by the sun.

Warnings: For external use only.

WHEN USING

Keep out of eyes. Rinse with water to remove.

STOP USE

Stop and ask a doctor if rash or irritation occurs.

Keep out of reach of children.

Directions:

- Apply liberally 15 minutes before sun exposure.
- Reapply: after swimming or sweating. Immediately after towel drying. At least every 2 hours.
- Children under 6 months: Ask a doctor.

INACTIVE INGREDIENT

Inactive Ingredients: Caprylic/Capric Triglyceride, Water (Aqua), Glycerin, Polysorbate 60, Stearic Acid, Cetyl Alcohol, Sorbitan Stearate, Cetearyl Glucoside, Stearyl Alcohol, Polyhydroxystearic Acid, Polyglyceryl-3 Ricinoleate, Isostearic Acid, Lecithin, Phenoxyethanol, Xanthan Gum, Carageenan, Helionori, Punica Granatum (Pomegranate) Extract, Plantago Lanceolate (Plantain) Leaf Extract, Ascorbyl Palmitate (Vitamin-C), Ethylhexylglycerin.

OTHER SAFETY INFORMATION

High sun protection product.

Questions? Call toll free 1-800-798-7970

PACKAGE LABEL

Sun Research LLC

Santa Cruz, CA

www.burnoutsun.com